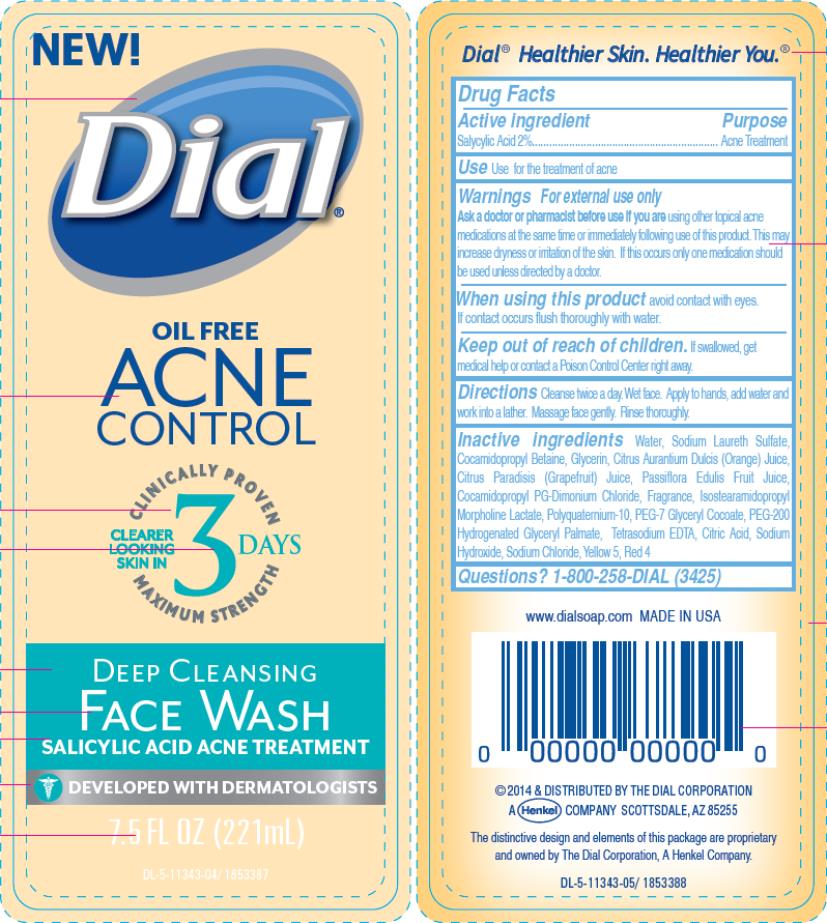 DRUG LABEL: Dial Acne Control Deep Cleansing Face Wash
NDC: 54340-400 | Form: SOLUTION
Manufacturer: The Dial Corporation
Category: otc | Type: HUMAN OTC DRUG LABEL
Date: 20140701

ACTIVE INGREDIENTS: SALICYLIC ACID 20 mg/1 mL
INACTIVE INGREDIENTS: WATER; SODIUM LAURETH-3 SULFATE; COCAMIDOPROPYL BETAINE; GLYCERIN; ORANGE JUICE; GRAPEFRUIT JUICE; PASSIFLORA EDULIS FRUIT JUICE; COCAMIDOPROPYL PROPYLENE GLYCOL-DIMONIUM CHLORIDE; ISOSTEARAMIDOPROPYL MORPHOLINE LACTATE; POLYQUATERNIUM-10 (30000 MPA.S AT 2%); PEG-7 GLYCERYL COCOATE; PEG-200 HYDROGENATED GLYCERYL PALMATE; EDETATE SODIUM; CITRIC ACID MONOHYDRATE; SODIUM HYDROXIDE; SODIUM CHLORIDE; FD&C YELLOW NO. 5; FD&C RED NO. 4

Dial Acne Control Deep Cleansing Face Wash

Drug Facts

Active ingredient

Salicylic Acid 2%

Purpose

Acne Treatment

Use

Use for the treatment of acne

Warnings

For external use only

Ask a doctor or pharmacist before use if you are

using other topical acne medications at the same time or immediately following use of this product. This may increase dryness or irritation of the skin. If this occurs only one medication should be used unless directed by a doctor.

When using this product

avoid contact with eyes. If contact occurs flush thoroughly with water.

Keep out of reach of children.

If swallowed, get medical help or contact a Poison Control Center right away.

Directions

Cleanse twice a day. Wet face. Apply to hands, add water and work into a lather. Massage face gently. Rinse thoroughly.

Inactive ingredients

Water, Sodium Laureth Sulfate, Cocamidopropyl Betaine, Glycerin, Citrus Aurantium Dulcis (Orange) Juice, Citrus Paradisis (Grapefruit) Juice, Passiflora Edulis Fruit Juice, Cocamidopropyl PG-Dimonium Chloride, Fragrance, Isostearamidopropyl Morpholine Lactate, Polyquaternium-10, PEG-7 Glyceryl Cocoate, PEG-200 Hydrogenated Glyceryl Palmate, Tetrasodium EDTA, Citric Acid, Sodium Hydroxide, Sodium Chloride, Yellow 5, Red 4

Questions?

1-800-258-DIAL (3425)

www.dialsoap.com MADE IN USA

The distinctive design and elements of this package are proprietary and owned by The Dial Corporation, A Henkel Company.

Principal Display Panel

NEW!
Dial
OIL FREE
ACNE
CONTROL
CLINICALLY PROVEN
CLEARER LOOKING SKIN IN 3 DAYS
MAXIMUM STRENGTH
DEEP CLEANSING
FACE WASH
SALICYLIC ACID ACNE TREATMENT
DEVELOPED WITH DERMATOLOGISTS
7.5 FL OZ (221mL)